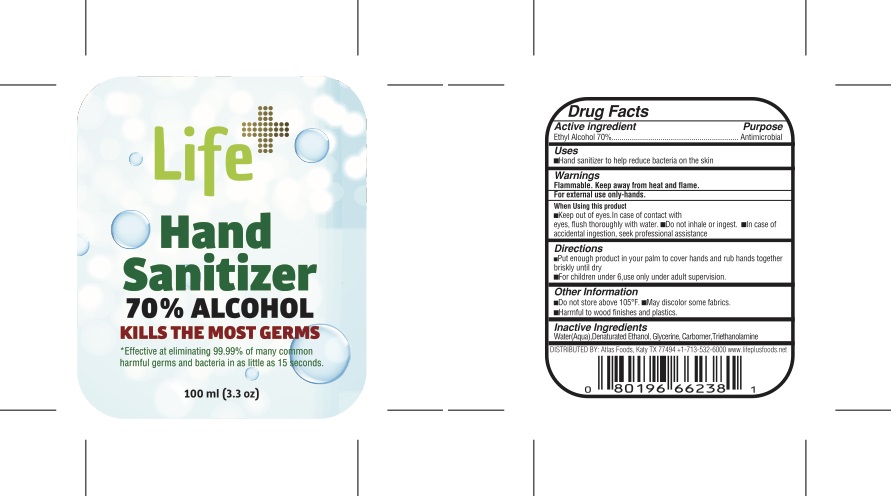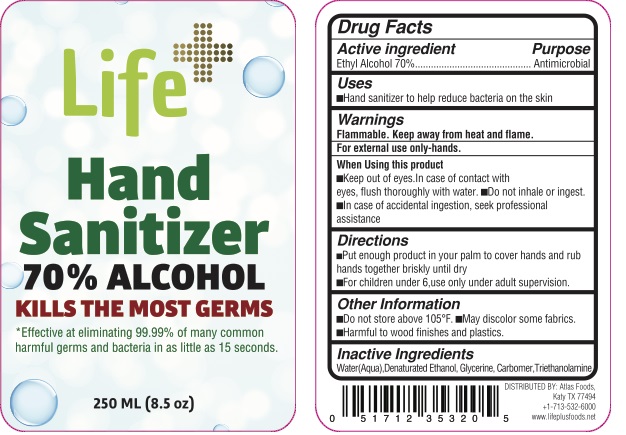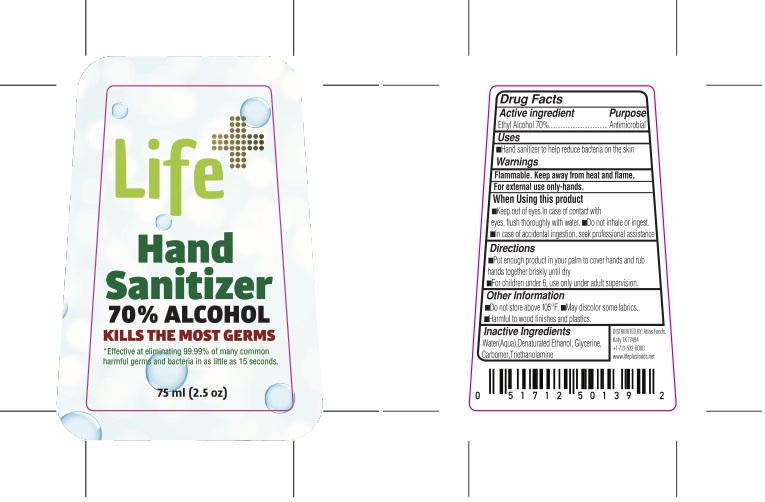 DRUG LABEL: 70% Alcohol kill the most germs
NDC: 76967-001 | Form: GEL
Manufacturer: LUKSEM PERAKENDE VE DIS TICARET ANONIM SIRKETI
Category: otc | Type: HUMAN OTC DRUG LABEL
Date: 20200428

ACTIVE INGREDIENTS: ALCOHOL 70 mL/100 mL
INACTIVE INGREDIENTS: WATER; CUPRIC TRIETHANOLAMINE; GLYCERIN; CARBOMER 1342

LIFE HAND SANITIZER

Active Ingredient

Ethyl Alcohol 70% v/v.

Purpose

Antimicrobial

Uses

Hand sanitizer to help decrease bacteria on the skin.

Warnings

For external use only-hands.

Flammable

Keep away from fire or flame

When using this product:

- Keep out of eyes.
- In case of contact with eyes, flush thoroughly with water.
- Do not inhale or ingest.
- In case of accidental ingestion ,seek professional assistance.

Directions

Place enough product on your palm to cover hands and rub hands together until dry.

For children under 6 years of age use only under adult Supervision.

Other information

- Do not store above 105℉
- May discolor some fabrics
- Harmful to wood finishes and plastics

Inactive ingredients

DENATURATED TRIETHANOLAMINE,WATER,GLYCERIN,CARBOMER 1342